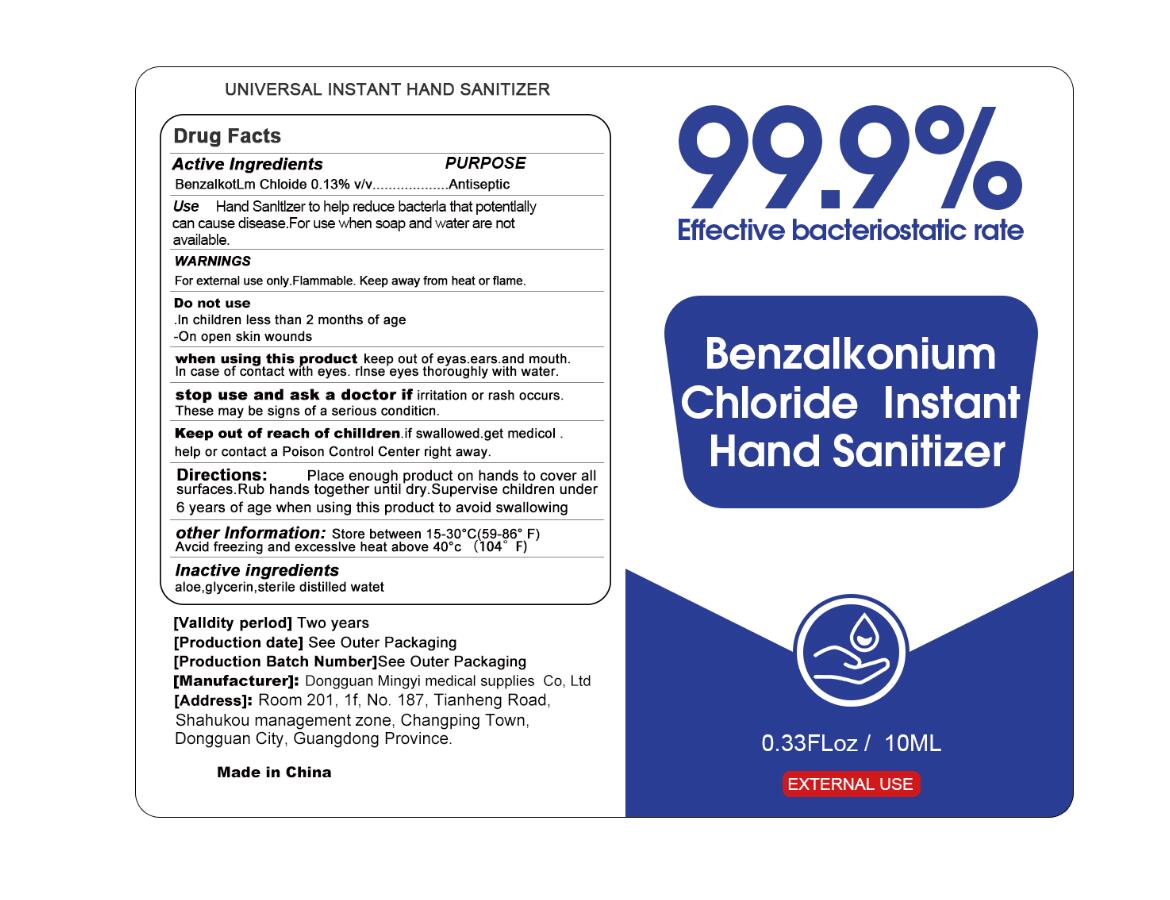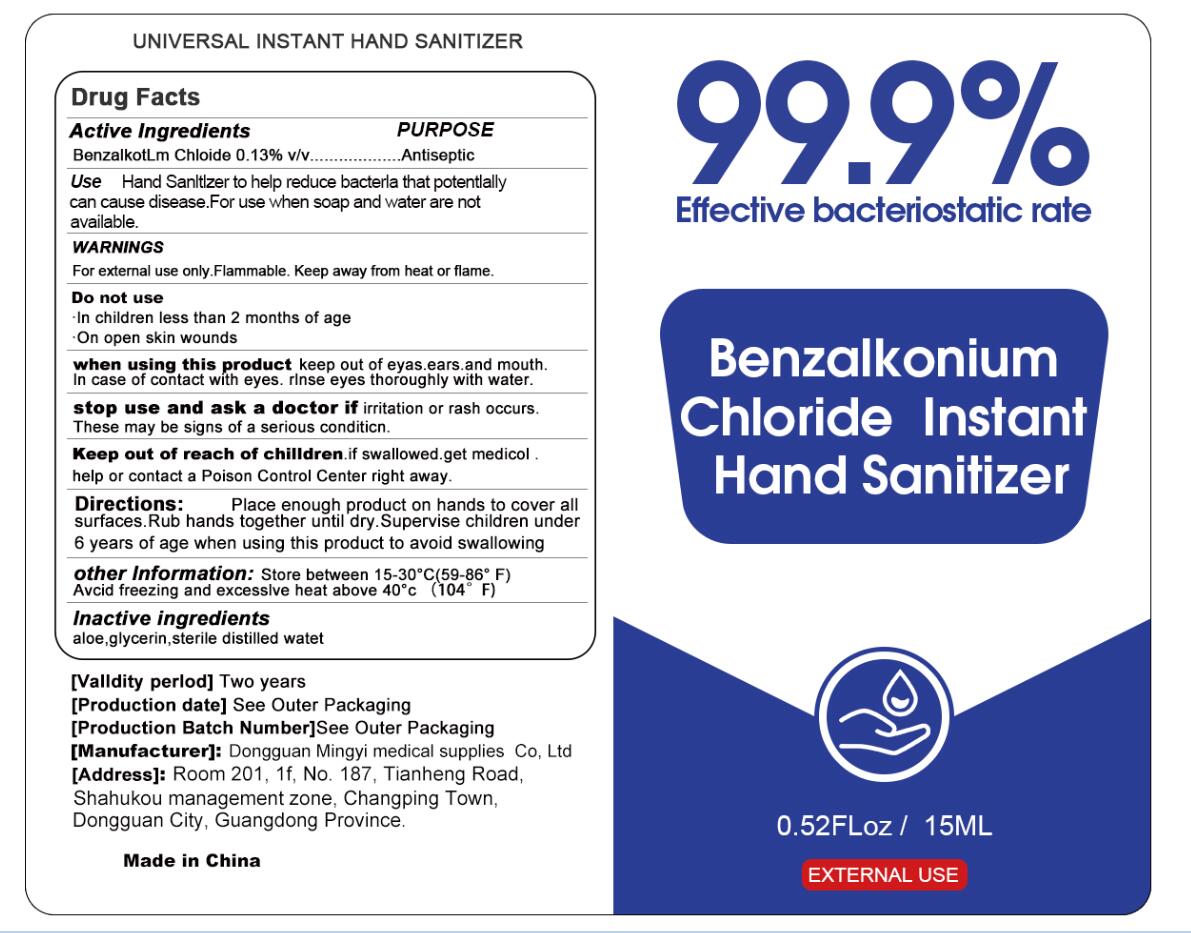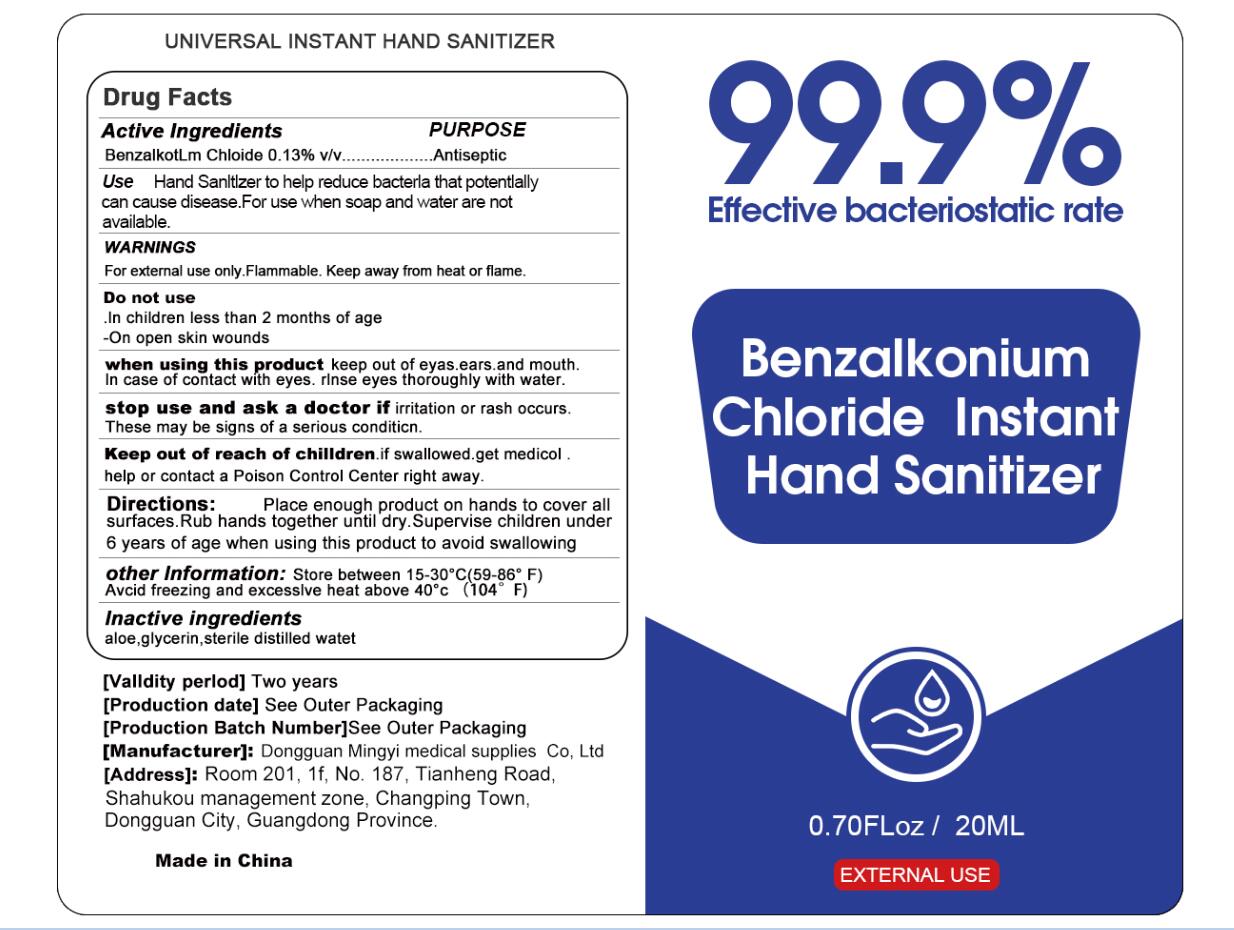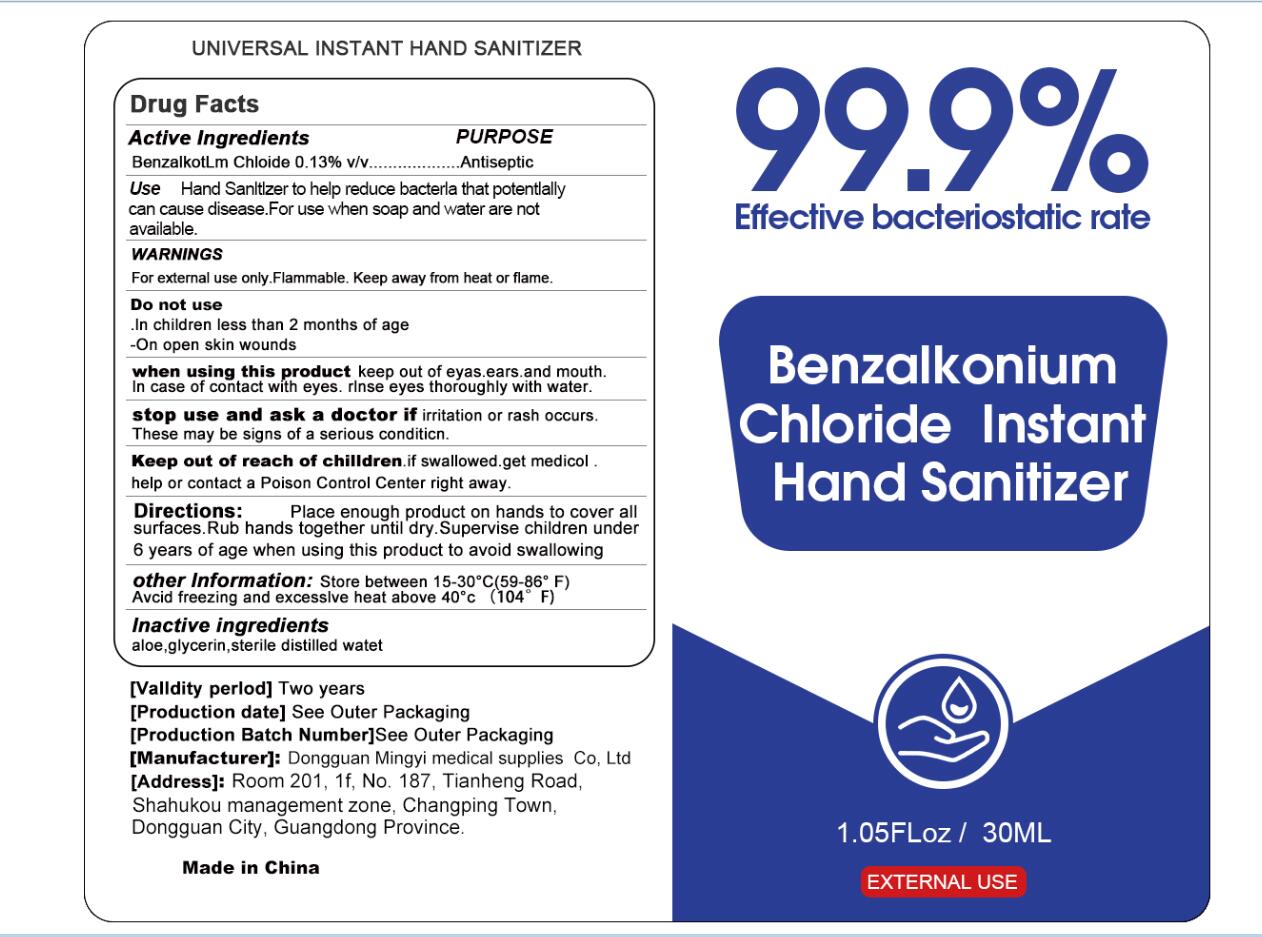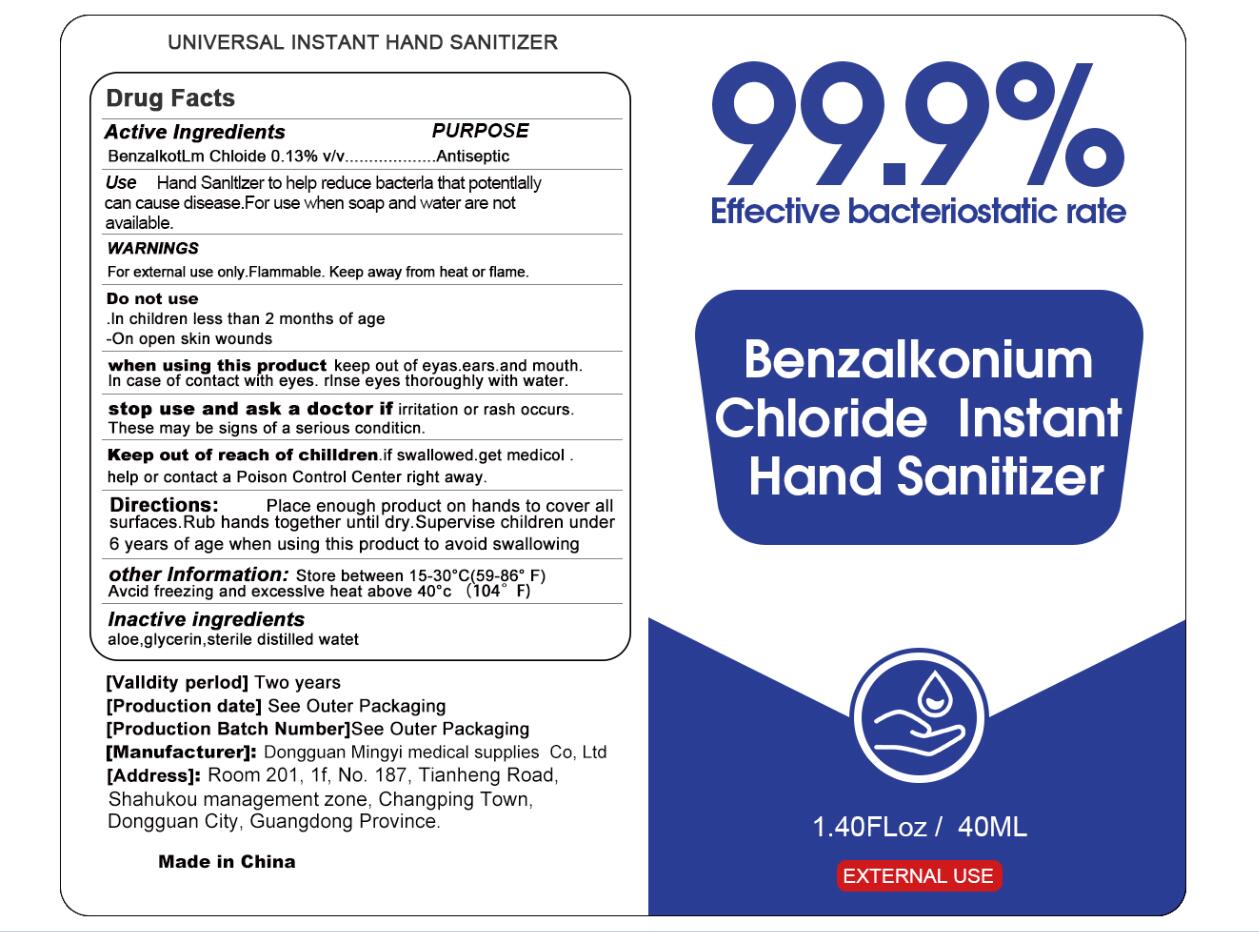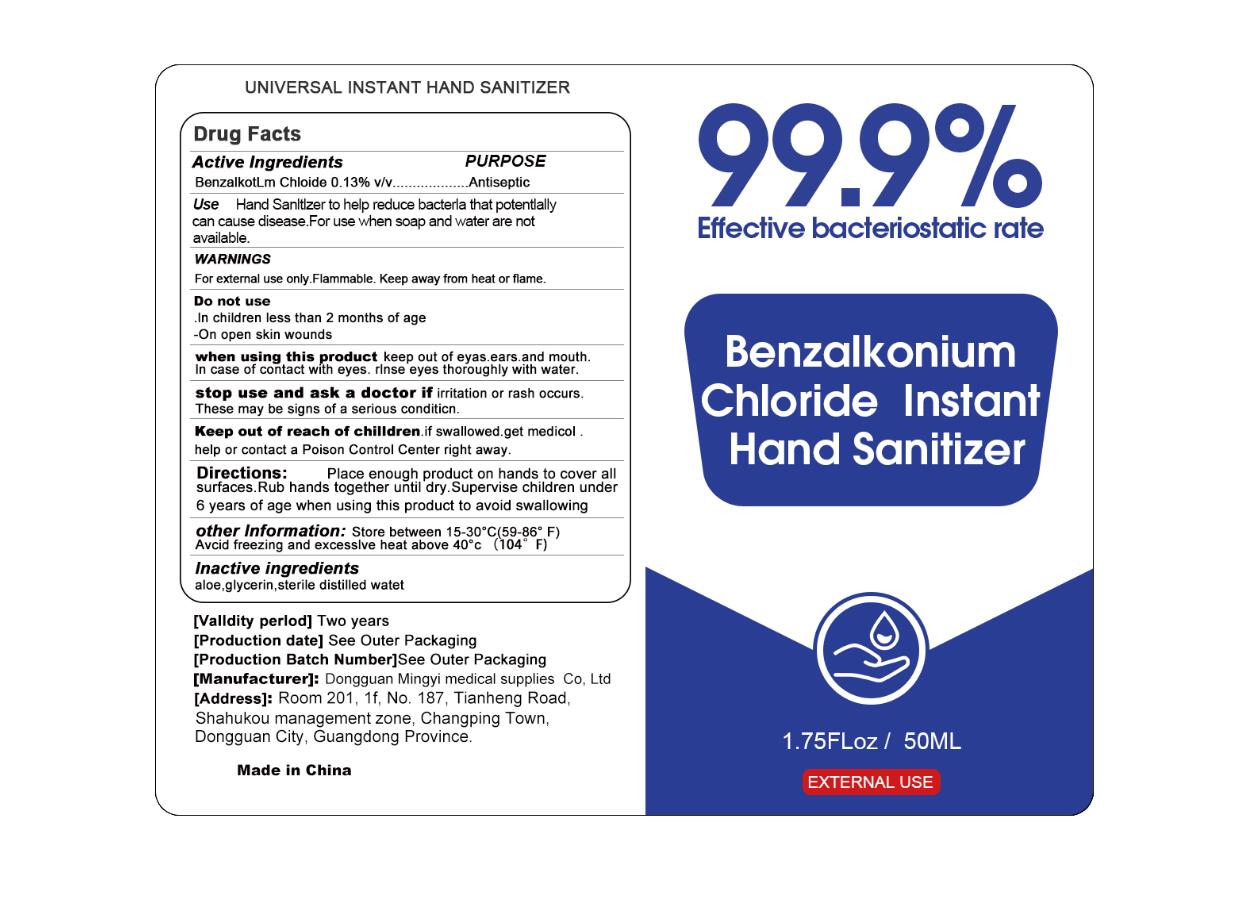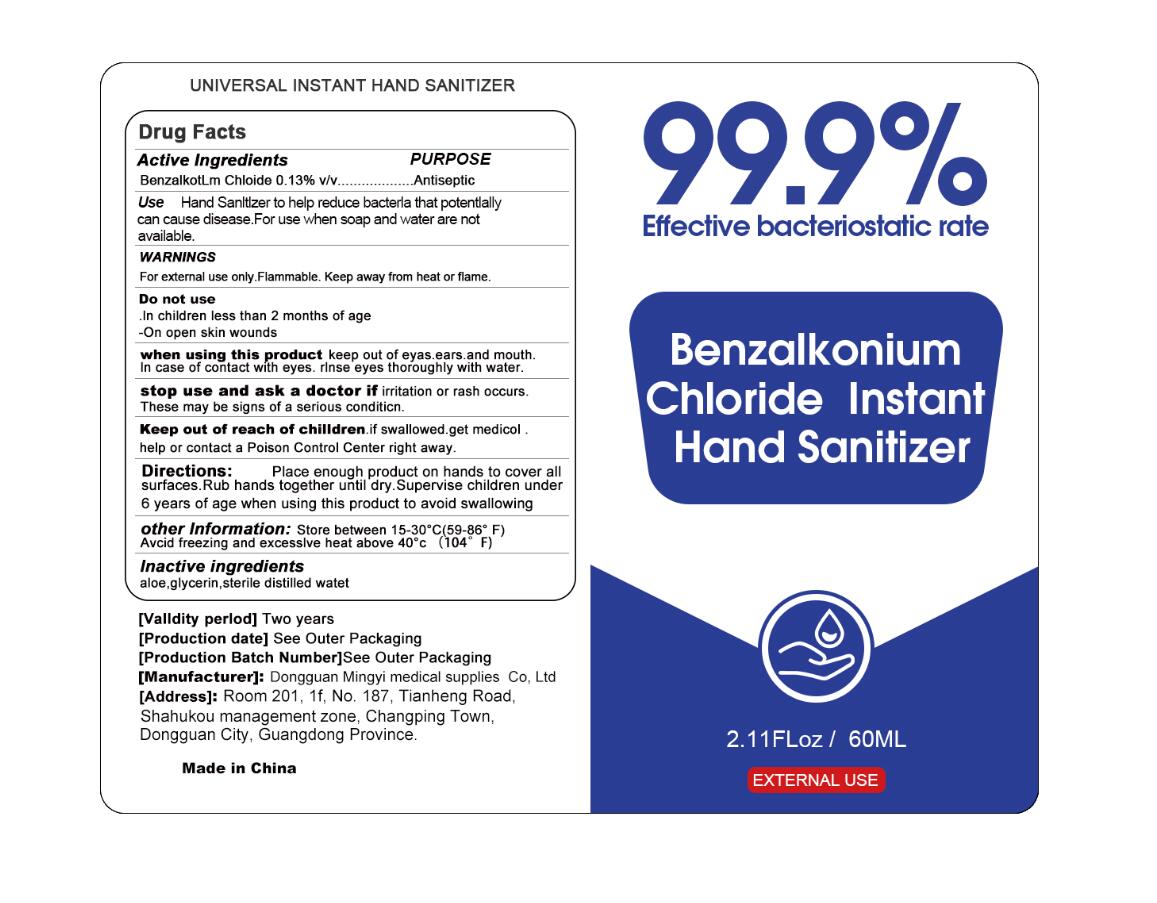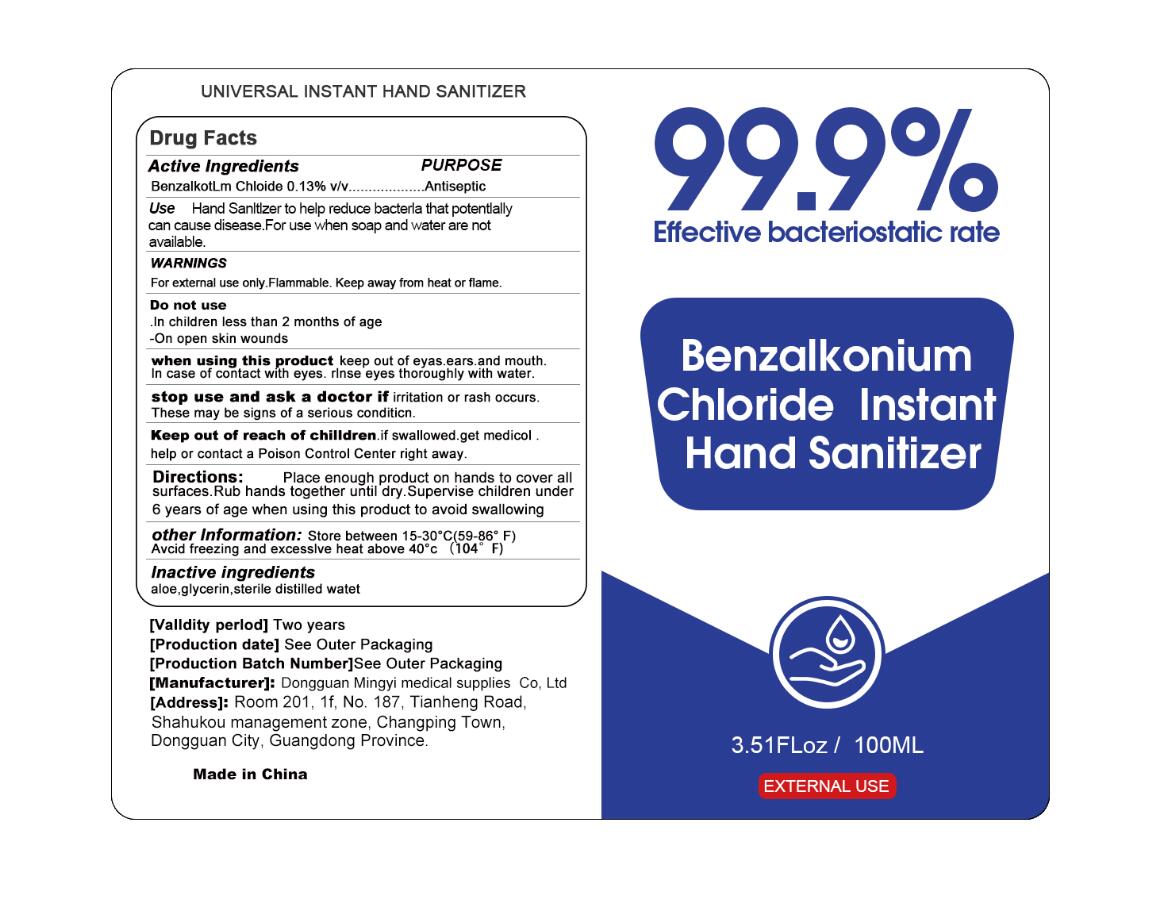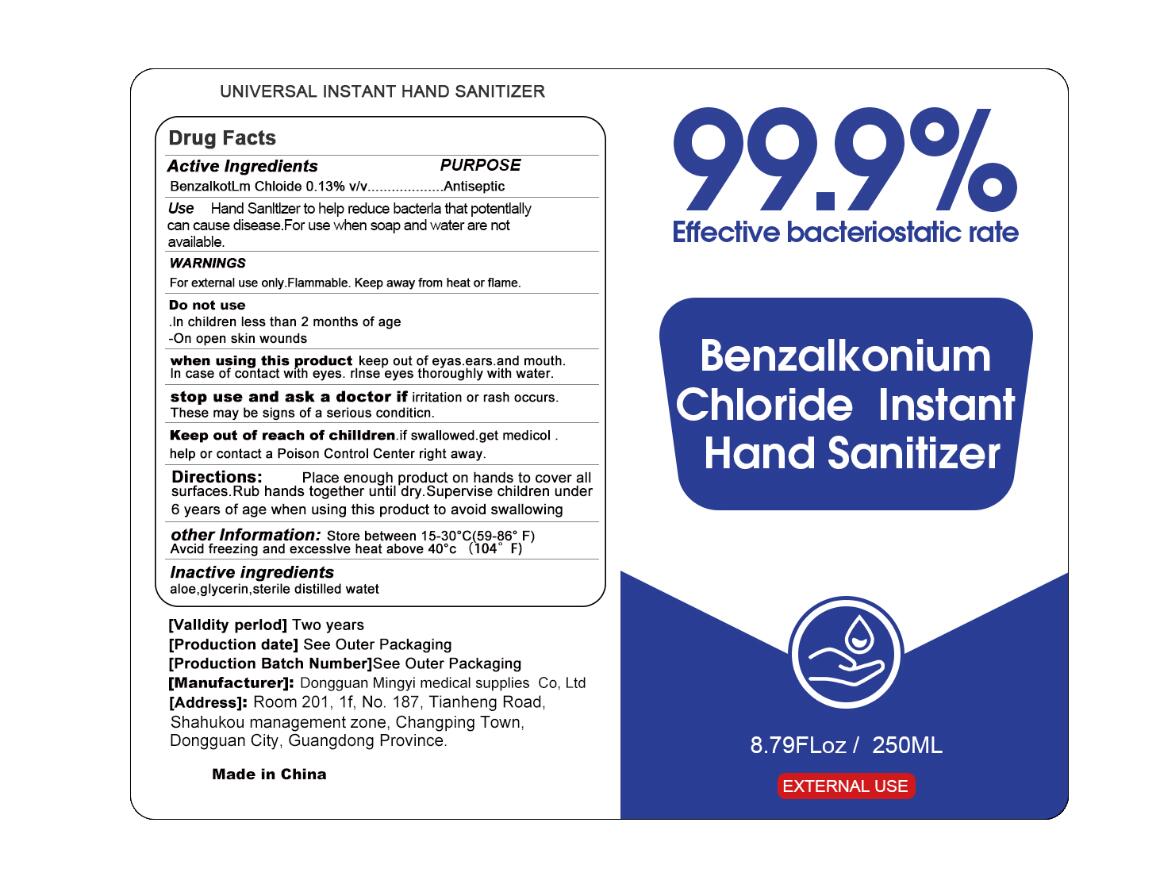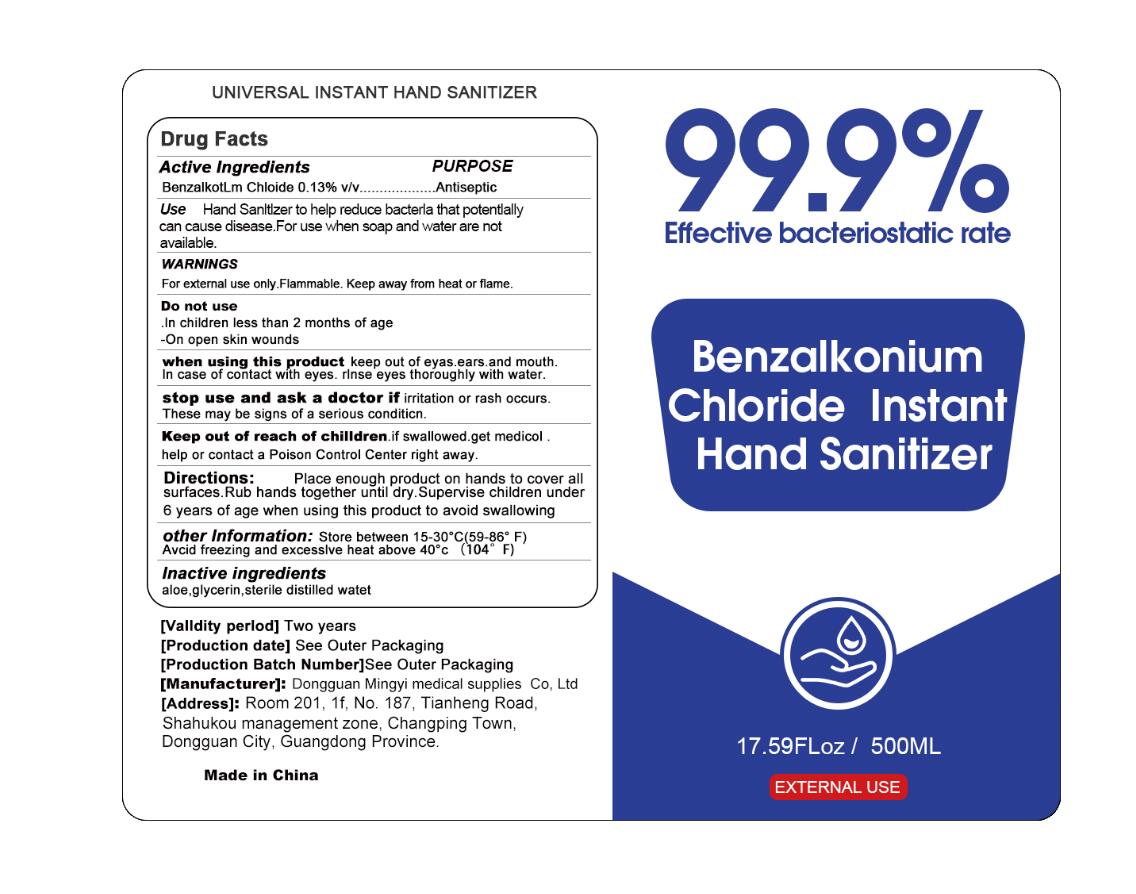 DRUG LABEL: Benzalkonium Chloride Instant Hand Sanitizer
NDC: 74046-006 | Form: LIQUID
Manufacturer: Dongguan Mingyi Medical Products  Co., Ltd.
Category: otc | Type: HUMAN OTC DRUG LABEL
Date: 20220304

ACTIVE INGREDIENTS: BENZALKONIUM CHLORIDE 0.13 g/100 mL
INACTIVE INGREDIENTS: WATER; GLYCERIN; ALOE

74046-006
Benzalkonium Chloride Instant Hand Sanitizer

Active Ingredients

Benzalkotlm Chloide 0.13% v/v

Purpose

Antiseptic

Uses

Hand Sanitizer to help reduce bacteria that potentially can cause disease. For use when soap and water are not available.

Warnings

For external use only. Flammable. Keep away from heat or flame.

Do not use

- In children less than 2 months of age

- On open skin wounds

when using this product

keep out of eyas, ears, and mouth, In case of contact with eyes . rinse eyes thoroughly with water.

stop use and ask a doctor if

irritation or rash occurs. These may be signs of a serious condition.

Directions

Place enough product on hands to cover all surfaces. Rub hands together until dry. Supervise children under 6 years of age when using this product to avoid swallowing

Other Information

Store between 15-30℃ (59-86℉)

Avcid freezing and excessive heat above 40℃ (104℉)

Inactive Ingredients

aloe , glycerin , sterile distilled watet